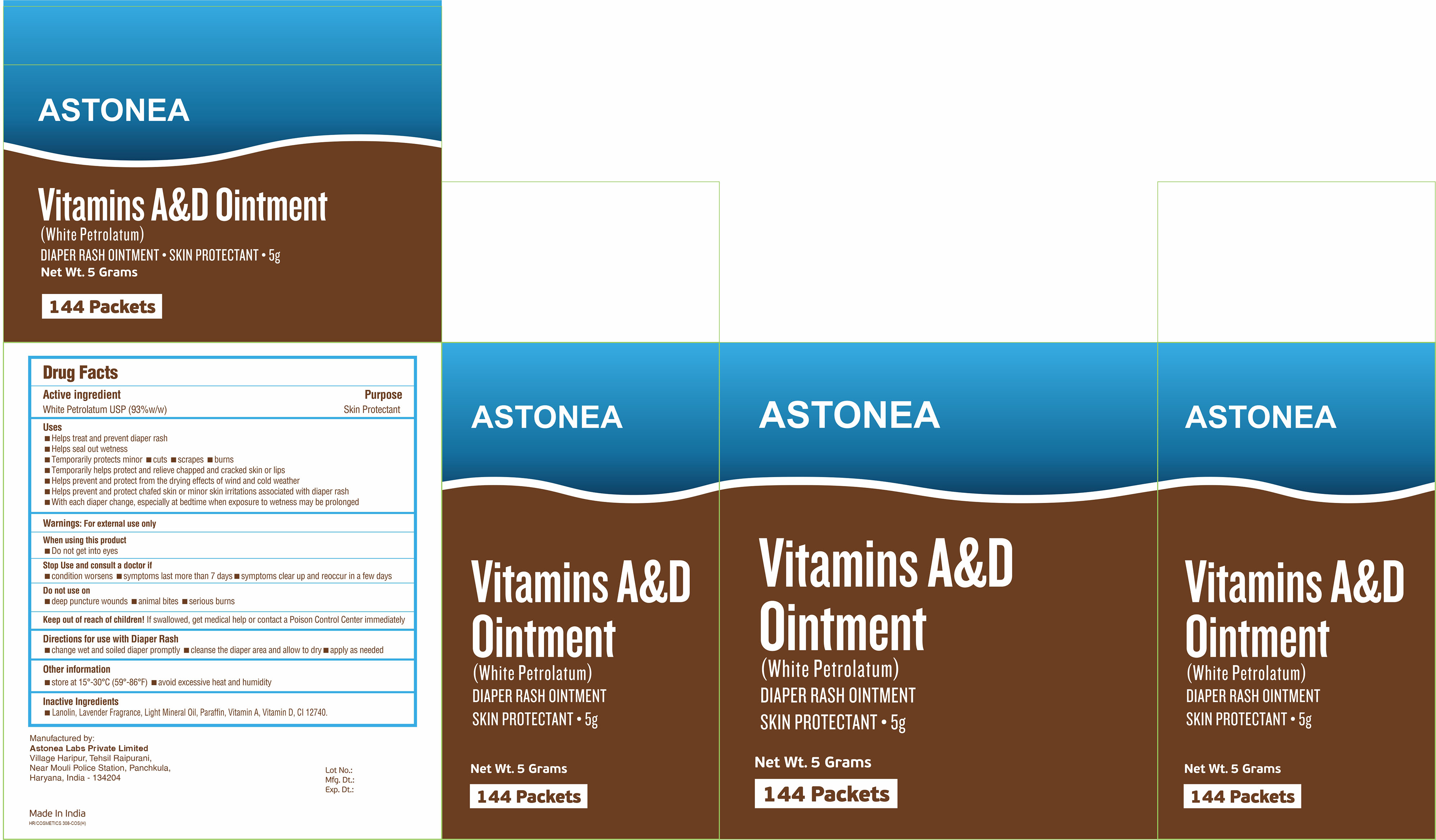 DRUG LABEL: Astonea 93-Vitamins A and D
NDC: 77338-115 | Form: OINTMENT
Manufacturer: ASTONEA LABS PRIVATE LIMITED
Category: otc | Type: HUMAN OTC DRUG LABEL
Date: 20221204

ACTIVE INGREDIENTS: PETROLATUM 0.93 g/1 g
INACTIVE INGREDIENTS: SOLVENT YELLOW 18; LANOLIN; PARAFFIN; LIGHT MINERAL OIL; VITAMIN A; VITAMIN D

Vitamins A and D 93 %

Drug Facts

Active ingredient

White Petrolatum USP (93%w/w)

Purpose

Skin Protectant

Uses

- Helps treat and prevent diaper rash
- Helps seal out wetness
- Temporarily protects minor
  - cuts
  - scrapes
  - burns
- Temporarily helps protect and relieve chapped and cracked skin or lips
- Helps prevent and protect from the drying effects of wind and cold weather
- Helps prevent and protect chafed skin or minor skin irritations associated with diaper rash
- With each diaper change, especially at bedtime when exposure to wetness may be prolonged

Warnings

For external use only

When using this product

- Do not get into eyes

Stop Use and consult a doctor if

- condition worsens
- symptoms last more than 7 days
- symptoms clear up and reoccur in a few days

Do not use on

- deep puncture wounds
- animal bites
- serious burns

Keep out of reach of children! If swallowed, get medical help or contact a Poison Control Center immediately

Directions for use with Diaper Rash

- change wet and soiled diaper promptly
- cleanse the diaper area and allow to dry
- apply as needed

Other information

- store at 15°-30°C (59°-86°F)
- avoid excessive heat and humidity

Inactive Ingredients

- Lanolin, Lavender Fragrance, Light Liquid Paraffin,Paraffin, Vitamin A, Vitamin D, CI 12740